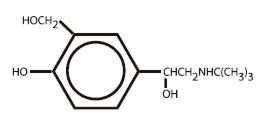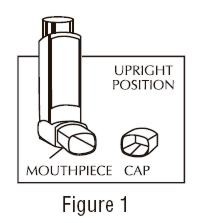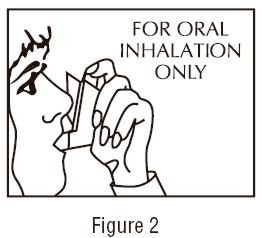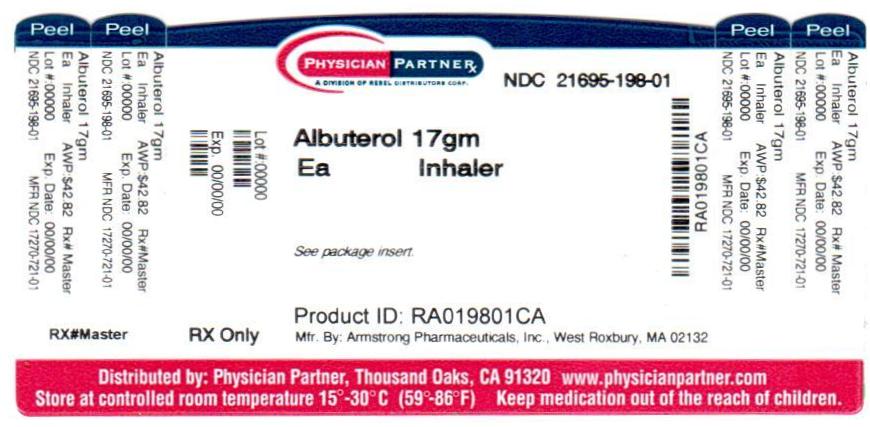 DRUG LABEL: Albuterol
NDC: 21695-198 | Form: AEROSOL, METERED
Manufacturer: Rebel Distributors Corp
Category: prescription | Type: HUMAN PRESCRIPTION DRUG LABEL
Date: 20110720

ACTIVE INGREDIENTS: Albuterol 90 ug/1 1
INACTIVE INGREDIENTS: TRICHLOROMONOFLUOROMETHANE 60.9 mg/1 1; dichlorofluoromethane 25.97 mg/1 1; oleic acid 0.011 mg/1 1

Albuterol
Inhalation Aerosol

Bronchodilator Aerosol
For Oral Inhalation Only

Rx only

DESCRIPTION

The active component of Albuterol Inhalation Aerosol is albuterol (α^1-[(tert-butylamino)methyl]-4-hydroxy-m-xylene-α,α'-diol), a relatively selective beta2-adrenergic bronchodilator, having the following structural formula:

Albuterol is the official generic name in the United States. The World Health Organization recommended name for the drug is salbutamol. The molecular weight of albuterol is 239.2, and the molecular formula is C13H21NO3. Albuterol is a white to off-white crystalline solid. It is soluble in ethanol, sparingly soluble in water, and very soluble in chloroform.

Albuterol Inhalation Aerosol is a pressurized metered-dose aerosol unit for oral inhalation. It contains a microcrystalline (95% ≤ 10 µm) suspension of albuterol in propellants (trichloromonofluoromethane and dichlorodifluoromethane) with oleic acid. Each actuation delivers 100 mcg of albuterol from the valve and 90 mcg of albuterol from the mouthpiece. Each canister provides 200 inhalations.

CLINICAL PHARMACOLOGY

In vitro studies and in vivo pharmacologic studies have demonstrated that albuterol has a preferential effect on beta2-adrenergic receptors compared with isoproterenol. While it is recognized that beta2-adrenergic receptors are the predominant receptors in bronchial smooth muscle, data indicate that there is a population of beta2-receptors in the human heart existing in a concentration between 10% and 50%. The precise function of these receptors has not been established.

The pharmacologic effects of beta-adrenergic agonist drugs, including albuterol, are at least in part attributable to stimulation through beta-adrenergic receptors of intracellular adenyl cyclase, the enzyme that catalyzes the conversion of adenosine triphosphate (ATP) to cyclic-3', 5'- adenosine monophosphate (cyclic AMP). Increased cyclic AMP levels are associated with relaxation of bronchial smooth muscle and inhibition of release of mediators of immediate hypersensitivity from cells, especially from mast cells.

Albuterol has been shown in most controlled clinical trials to have more effect on the respiratory tract, in the form of bronchial smooth muscle relaxation, than isoproterenol at comparable doses while producing fewer cardiovascular effects. Controlled clinical studies and other clinical experience have shown that inhaled albuterol, like other beta-adrenergic agonist drugs, can produce a significant cardiovascular effect in some patients, as measured by pulse rate, blood pressure, symptoms, and/or electrocardiographic changes.

Albuterol is longer acting than isoproterenol in most patients by any route of administration because it is not a substrate for the cellular uptake processes for catecholamines nor for catechol-O-methyl transferase.

The effects of rising doses of albuterol and isoproterenol aerosols were studied in volunteers and asthmatic patients. Results in normal volunteers indicated that albuterol is one half to one quarter as active as isoproterenol in producing increases in heart rate. In asthmatic patients similar cardiovascular differentiation between the two drugs was also seen.

Preclinical

Intravenous studies in rats with albuterol sulfate have demonstrated that albuterol crosses the blood brain barrier and reaches brain concentrations amounting to approximately 5.0% of the plasma concentrations. In structures outside the brain barrier (pineal and pituitary glands), albuterol concentrations were found to be 100 times those in the whole brain.

Studies in laboratory animals (minipigs, rodents, and dogs) have demonstrated the occurrence of cardiac arrhythmias and sudden death (with histologic evidence of myocardial necrosis) when beta-agonists and methylxanthines are administered concurrently. The clinical significance of these findings is unknown.

Pharmacokinetics

Because of its gradual absorption from the bronchi, systemic levels of albuterol are low after inhalation of recommended doses. Studies undertaken with four subjects administered tritiated albuterol resulted in maximum plasma concentrations occurring within two to four hours. Due to the sensitivity of the assay method, the metabolic rate and half-life of elimination of albuterol in plasma could not be determined. However, urinary excretion provided data indicating that albuterol has an elimination half-life of 3.8 hours. Approximately 72% of the inhaled dose is excreted within 24 hours in the urine, and consists of 28% as unchanged drug and 44% as metabolite.

Clinical Trials

In controlled clinical trials involving adults with asthma, the onset of improvement in pulmonary function was within 15 minutes, as determined by both MMEF (maximum midexpiratory flow rate) and FEV1 (forced expiratory volume in one second). MMEF measurements also showed that near maximum improvement in pulmonary function generally occurs within 60 to 90 minutes following two inhalations of albuterol and that clinically significant improvement generally continues for three to four hours in most patients. Some patients showed a therapeutic response (defined by maintaining FEV1 values 15% or more above baseline) that was still apparent at 6 hours. Continued effectiveness of albuterol was demonstrated over a 13-week period in these same trials.

In controlled clinical trials involving children 4 to 12 years of age, FEV1 measurements showed that maximum improvement in pulmonary function occurs within 30 to 60 minutes. The onset of clinically significant (≥15%) improvement in FEV1 was observed as soon as five minutes following 180 mcg of albuterol in 18 of 30 (60%) children in a controlled dose-ranging study. Clinically significant improvement in FEV1 continued in the majority of patients for two hours and in 33% to 47% for four hours among 56 patients receiving inhalation aerosol in one pediatric study. In a second study among 48 patients receiving inhalation aerosol, clinically significant improvement continued in the majority for up to one hour and in 23% to 40% for four hours. In addition, at least 50% of the patients in both studies achieved an improvement in FEF25%–75% (forced expiratory flow rate between 25% and 75% of the forced vital capacity) of at least 20% for 2 to 5 hours. Continued effectiveness of albuterol was demonstrated over the 12-week study period.

In other clinical studies in adults and children, two inhalations of albuterol aerosol taken approximately 15 minutes before exercise prevented exercise-induced bronchospasm, as demonstrated by the maintenance of FEV1 within 80% of baseline values in the majority of patients. One study in adults also evaluated the duration of the prophylactic effect to repeated exercise challenges, which was evident at 4 hours in a majority of the patients and at 6 hours in approximately one third of the patients.

INDICATIONS AND USAGE

Albuterol Inhalation Aerosol is indicated for the prevention and relief of bronchospasm in patients 4 years of age and older with reversible obstructive airway disease, and for the prevention of exercise induced bronchospasm in patients 4 years of age and older.

Albuterol Inhalation Aerosol can be used with or without concomitant steroid therapy.

CONTRAINDICATIONS

Albuterol Inhalation Aerosol is contraindicated in patients with a history of hypersensitivity to albuterol or any of its components.

WARNINGS

Paradoxical Bronchospasm

Albuterol can produce paradoxical bronchospasm, which may be life threatening. If paradoxical bronchospasm occurs, Albuterol Inhalation Aerosol should be discontinued immediately and alternative therapy instituted. It should be recognized that paradoxical bronchospasm, when associated with inhaled formulations, frequently occurs with the first use of a new canister or vial.

Cardiovascular Effects

Albuterol, like all other beta-adrenergic agonists, can produce a clinically significant cardiovascular effect in some patients as measured by pulse rate, blood pressure, and/or symptoms. Although such effects are uncommon after administration of Albuterol Inhalation Aerosol at recommended doses, if they occur, the drug may need to be discontinued. In addition, beta-agonists have been reported to produce electrocardiogram (ECG) changes, such as flattening of the T wave, prolongation of the QTc interval, and ST segment depression. The clinical significance of these findings is unknown. Therefore, albuterol, like all sympathomimetic amines, should be used with caution in patients with cardiovascular disorders, especially coronary insufficiency, cardiac arrhythmias, and hypertension.

Deterioration of Asthma

Asthma may deteriorate acutely over a period of hours or chronically over several days or longer. If the patient needs more doses of Albuterol Inhalation Aerosol than usual, this may be a marker of destabilization of asthma and requires reevaluation of the patient and treatment regimen, giving special consideration to the possible need for anti-inflammatory treatment, e.g., corticosteroids.

Use of Anti-Inflammatory Agents

The use of beta-adrenergic agonist bronchodilators alone may not be adequate to control asthma in many patients. Early consideration should be given to adding anti-inflammatory agents, e.g., corticosteroids.

Immediate hypersensitivity reactions may occur after administration of Albuterol Inhalation Aerosol, as demonstrated by rare cases of urticaria, angioedema, rash, bronchospasm, anaphylaxis, and oropharyngeal edema.

The contents of Albuterol Inhalation Aerosol are under pressure. Do not puncture. Do not use or store near heat or open flame. Exposure to temperatures above 120°F may cause bursting. Never throw container into fire or incinerator. Avoid spraying in eyes. Keep out of reach of children.

PRECAUTIONS

General

Albuterol, as with all sympathomimetic amines, should be used with caution in patients with cardiovascular disorders, especially coronary insufficiency, cardiac arrhythmias, and hypertension; in patients with convulsive disorders, hyperthyroidism, or diabetes mellitus; and in patients who are unusually responsive to sympathomimetic amines. Clinically significant changes in systolic and diastolic blood pressure have been seen in individual patients and could be expected to occur in some patients after use of any beta-adrenergic bronchodilator.

Large doses of intravenous albuterol have been reported to aggravate preexisting diabetes mellitus and ketoacidosis. As with other beta-agonists, albuterol may produce significant hypokalemia in some patients, possibly through intracellular shunting, which has the potential to produce adverse cardiovascular effects. The decrease is usually transient, not requiring supplementation.

Although there have been no reports concerning the use of Albuterol Inhalation Aerosol during labor and delivery, it has been reported that high doses of albuterol administered intravenously inhibit uterine contractions. Although this effect is extremely unlikely as a consequence of aerosol use, it should be kept in mind.

Information for Patients

The action of Albuterol Inhalation Aerosol may last up to six hours or longer. Albuterol Inhalation Aerosol should not be used more frequently than recommended. Do not increase the dose or frequency of Albuterol Inhalation Aerosol without consulting your physician. If you find that treatment with Albuterol Inhalation Aerosol becomes less effective for symptomatic relief, your symptoms become worse, and/or you need to use the product more frequently than usual, you should seek medical attention immediately. While you are using Albuterol Inhalation Aerosol, other inhaled drugs and asthma medications should be taken only as directed by your physician. Common adverse effects include palpitations, chest pain, rapid heart rate, and tremor or nervousness. If you are pregnant or nursing, contact your physician about use of Albuterol Inhalation Aerosol. Effective and safe use of Albuterol Inhalation Aerosol includes an understanding of the way that it should be administered.

In general, the technique for administering Albuterol Inhalation Aerosol to children is similar to that for adults, since children's smaller ventilatory exchange capacity automatically provides proportionally smaller aerosol intake. Children should use Albuterol Inhalation Aerosol under adult supervision, as instructed by the patient's physician.

See illustrated Patient's Instructions for Use.

Drug Interactions

Other short-acting sympathomimetic aerosol bronchodilators should not be used concomitantly with albuterol. If additional adrenergic drugs are to be administered by any route, they should be used with caution to avoid deleterious cardiovascular effects.

Monoamine Oxidase Inhibitors or Tricyclic Antidepressants

Albuterol should be administered with extreme caution to patients being treated with monoamine oxidase inhibitors or tricyclic antidepressants, or within two weeks of discontinuation of such agents, because the action of albuterol on the vascular system may be potentiated.

Beta-Blockers

Beta-adrenergic receptor blocking agents not only block the pulmonary effect of beta-agonists, such as albuterol, but may produce severe bronchospasm in asthmatic patients. Therefore, patients with asthma should not normally be treated with beta-blockers. However, under certain circumstances, e.g., as prophylaxis after myocardial infarction, there may be no acceptable alternatives to the use of beta-adrenergic blocking agents in patients with asthma. In this setting, cardioselective beta-blockers should be considered, although they should be administered with caution.

Diuretics

The ECG changes and/or hypokalemia that may result from the administration of nonpotassium-sparing diuretics (such as loop or thiazide diuretics) can be acutely worsened by beta-agonists, especially when the recommended dose of the beta-agonist is exceeded. Although the clinical significance of these effects is not known, caution is advised in the coadministration of beta-agonists with nonpotassium-sparing diuretics.

Digoxin

Mean decreases of 16% to 22% in serum digoxin levels were demonstrated after single-dose intravenous and oral administration of albuterol, respectively, to normal volunteers who had received digoxin for 10 days. The clinical significance of these findings for patients with obstructive airway disease who are receiving albuterol and digoxin on a chronic basis is unclear. Nevertheless, it would be prudent to carefully evaluate the serum digoxin levels in patients who are currently receiving digoxin and albuterol.

Carcinogenesis, Mutagenesis, Impairment of Fertility

In a two-year study in Sprague-Dawley rats, albuterol sulfate caused a significant dose-related increase in the incidence of benign leiomyomas of the mesovarium at dietary doses of 2.0, 10, and 50 mg/kg (approximately 15, 70, and 340 times, respectively, the maximum recommended daily inhalation dose for adults on a mg/m^2 basis, or, approximately 6, 30, and 160 times, respectively, the maximum recommended daily inhalation dose in children on a mg/m^2 basis). In another study this effect was blocked by the coadministration of propranolol, a non-selective beta-adrenergic antagonist. In an 18-month study in CD-1 mice, albuterol sulfate showed no evidence of tumorigenicity at dietary doses of up to 500 mg/kg (approximately 1700 times the maximum recommended daily inhalation dose for adults on a mg/m^2 basis, or, approximately 800 times the maximum recommended daily inhalation dose for children on a mg/m^2 basis). In a 22-month study in the Golden hamster, albuterol sulfate showed no evidence of tumorigenicity at dietary doses of up to 50 mg/kg (approximately 225 times the maximum recommended daily inhalation dose for adults on a mg/m^2 basis, or, approximately 110 times the maximum recommended daily inhalation dose for children on a mg/m^2 basis).

Albuterol sulfate was not mutagenic in the Ames test with or without metabolic activation using tester strains S. typhimurium TA1537, TA1538, and TA98 or E. Coli WP2, WP2uvrA, and WP67. No forward mutation was seen in yeast strain S. cerevisiae S9 nor any mitotic gene conversion in yeast strain S. cerevisiae JD1 with or without metabolic activation. Fluctuation assays in S. typhimurium TA98 and E.Coli WP2, both with metabolic activation, were negative. Albuterol sulfate was not clastogenic in a human peripheral lymphocyte assay or in an AH1 strain mouse micronucleus assay at intraperitoneal doses of up to 200 mg/kg.

Reproduction studies in rats demonstrated no evidence of impaired fertility at oral doses of up to 50 mg/kg (approximately 340 times the maximum recommended daily inhalation dose for adults on a mg/m^2 basis).

Pregnancy

Teratogenic Effects

Pregnancy Category C

Albuterol sulfate has been shown to be teratogenic in mice. A study in CD-1 mice at subcutaneous (sc) doses of 0.025, 0.25, and 2.5 mg/kg (approximately 2/25, 1.0, and 8.0 times, respectively, the maximum recommended daily inhalation dose for adults on a mg/m^2 basis), showed cleft palate formation in 5 of 111 (4.5%) fetuses at 0.25 mg/kg and in 10 of 108 (9.3%) fetuses at 2.5 mg/kg. The drug did not induce cleft palate formation at the lowest dose, 0.025 mg/kg. Cleft palate also occurred in 22 of 72 (30.5%) fetuses from females treated with 2.5 mg/kg of isoproterenol (positive control) sc (approximately 8 times the maximum recommended daily inhalation dose for adults on a mg/m^2 basis).

A reproduction study in Stride Dutch rabbits revealed cranioschisis in 7 of 19 (37%) fetuses when albuterol sulfate was administered orally at a 50 mg/kg dose (approximately 680 times the maximum recommended daily inhalation dose for adults on a mg/m^2 basis). There are no adequate and well-controlled studies in pregnant women. Albuterol should be used during pregnancy only if the potential benefit justifies the potential risk to the fetus.

During worldwide marketing experience, various congenital anomalies, including cleft palate and limb defects, have been rarely reported in the offspring of patients being treated with albuterol. Some of the mothers were taking multiple medications during their pregnancies. No consistent pattern of defects can be discerned, and a relationship between albuterol use and congenital anomalies has not been established.

Use in Labor and Delivery

Because of the potential for beta-agonist interference with uterine contractility, use of albuterol for relief of bronchospasm during labor should be restricted to those patients in whom the benefits clearly outweigh the risk.

Tocolysis

Albuterol has not been approved for the management of preterm labor. The benefit:risk ratio when albuterol is administered for tocolysis has not been established. Serious adverse reactions, including maternal pulmonary edema, have been reported during or following treatment of premature labor with beta2-agonists, including albuterol.

Nursing Mothers

It is not known whether this drug is excreted in human milk. Because of the potential for tumorigenicity shown for albuterol in some animal studies, a decision should be made whether to discontinue nursing or to discontinue the drug, taking into account the importance of the drug to the mother.

Pediatric Use

Safety and effectiveness in pediatric patients below 4 years of age have not been established.

ADVERSE REACTIONS

The adverse reactions to albuterol are similar in nature to reactions to other sympathomimetic agents, although the incidence of certain cardiovascular effects is lower with albuterol.

Percent Incidence of Adverse Reactions in Patients ≥ 12 Years of Age in a 13-Week Clinical Trial [A 13-week double-blind study compared albuterol and isoproterenol inhalation aerosols in 147 asthmatic patients.]
 | Percent Incidence
Reaction | Albuterol | Isoproterenol
Tremor | <15% | <15%
Nausea | <15% | <15%
Tachycardia | 10% | 10%
Palpitations | <10% | <15%
Nervousness | <10% | <15%
Increased Blood Pressure | <5% | <5%
Dizziness | <5% | <5%
Heartburn | <5% | <5%

Percent Incidence of Adverse Reactions in Children 4 to 11 Years of Age in a 12-Week Trial [A 12-week double-blind trial in 104 patients aged 4 to 11 years.]
Reaction | Percent Incidence
Central Nervous System
Headache | 3%
Nervousness | 1%
Lightheadedness | <1%
Tremor | <1%
Agitation | 1%
Nightmares | 1%
Hyperactivity | 1%
Aggressive Behavior | 1%
Gastrointestinal
Nausea and/or Vomiting | 6%
Stomachache | 3%
Diarrhea | 1%
Oropharyngeal
Throat Irritation | 6%
Discoloration of Teeth | 1%
Respiratory
Epistaxis | 3%
Cough | 2%
Musculoskeletal
Muscle Cramp | 1%

Cases of urticaria, angioedema, rash, bronchospasm, hoarseness, oropharyngeal edema, and arrhythmias (including atrial fibrillation, supraventricular tachycardia, extrasystoles) have been reported after the use of albuterol inhalation aerosol.

In addition, albuterol, like other sympathomimetic agents, can cause adverse reactions such as hypertension, angina, vertigo, central nervous system stimulation, sleeplessness, and unusual taste.

OVERDOSAGE

The expected symptoms with overdosage are those of excessive beta-adrenergic stimulation and/or occurrence or exaggeration of any of the symptoms listed under ADVERSE REACTIONS, e.g., seizures, angina, hypertension, hypotension, tachycardia with rates up to 200 beats/minute, arrhythmias, nervousness, headache, tremor, dry mouth, palpitation, nausea, dizziness, fatigue, malaise, and sleeplessness. Hypokalemia may also occur.

As with all sympathomimetic aerosol medications, cardiac arrest and even death may be associated with abuse of Albuterol Inhalation Aerosol. Treatment consists of discontinuation of Albuterol Inhalation Aerosol together with appropriate symptomatic therapy. The judicious use of a cardioselective beta-receptor blocker may be considered, bearing in mind that such medication can produce bronchospasm. There is insufficient evidence to determine if dialysis is beneficial for overdosage of Albuterol Inhalation Aerosol.

The oral median lethal dose of albuterol sulfate in mice is greater than 2000 mg/kg (approximately 6800 times the maximum recommended daily inhalation dose for adults on a mg/m^2 basis, or, approximately 3200 times the maximum recommended daily inhalation dose for children on a mg/m^2 basis). In mature rats, the sc median lethal dose of albuterol sulfate is approximately 450 mg/kg (approximately 3000 times the maximum recommended daily inhalation dose for adults on a mg/m^2 basis, or, approximately 1400 times the maximum recommended daily inhalation dose for children on a mg/m^2 basis). In small young rats, the sc median lethal dose of albuterol sulfate is approximately 2000 mg/kg (approximately 14,000 times the maximum recommended daily inhalation dose for adults on a mg/m^2 basis, or, approximately 6400 times the maximum recommended daily inhalation dose for children on a mg/m^2 basis). The inhalation median lethal dose has not been determined in animals.

DOSAGE AND ADMINISTRATION

For treatment of acute episodes of bronchospasm or prevention of asthmatic symptoms, the usual dosage for adults and pediatric patients 4 years and older is two inhalations repeated every four to six hours; in some patients, one inhalation every four hours may be sufficient. More frequent administration or a larger number of inhalations are not recommended. It is recommended to "test spray" Albuterol Inhalation Aerosol into the air before using for the first time and in cases where the aerosol has not been used for a prolonged period of time.

The use of Albuterol Inhalation Aerosol can be continued as medically indicated to control recurring bouts of bronchospasm. During this time most patients gain optimal benefit from regular use of the inhaler. Safe usage for periods extending over several years has been documented.

If a previously effective dosage regimen fails to provide the usual response, this may be a marker of destabilization of asthma and requires reevaluation of the patient and the treatment regimen, giving special consideration to the possible need for anti-inflammatory treatment, e.g., corticosteroids.

Exercise-Induced Bronchospasm Prevention

The usual dosage for adults and pediatric patients 4 years and older is two inhalations 15 minutes before exercise.

For treatment, see above.

HOW SUPPLIED

Albuterol Inhalation Aerosol is supplied in 17 g canisters containing 200 metered inhalations (NDC 21695-198-01) in boxes of one. Each actuation delivers 100 mcg of albuterol from the valve and 90 mcg of albuterol from the mouthpiece. Each canister is supplied with a blue oral adapter and patient's instructions.

The blue adapter supplied with Albuterol Inhalation Aerosol should not be used with any other product canisters, and the adapters from other products should not be used with an Albuterol Inhalation Aerosol canister. The correct amount of medication in each canister cannot be assured after 200 actuations, even though the canister is not completely empty. The canister should be discarded when the labeled number of actuations have been used.

Store between 15°–30°C (59°–86°F). As with most inhaled medications in aerosol canisters, the therapeutic effect of this medication may decrease when the canister is cold; for best results, the canister should be at room temperature before use.

Shake well before using.

Note: The indented statement below is required by the Federal government Clean Air Act for all products containing chlorofluorocarbons (CFC's).

WARNING: This product contains trichloromonofluoro-methane and dichlorodifluoromethane (CFC's), substances which harm public health and environment by destroying ozone in the upper atmosphere.

A notice similar to the above warning has been placed in the patient instruction leaflet of this package insert pursuant to the regulations of the U.S. Environmental Protection Agency (EPA). The patient's warning states that the patient should consult his or her physician if there are questions about alternatives.

Rx only.

Manufactured by

Armstrong Pharmaceuticals, Inc.
West Roxbury, MA 02132
An Amphastar Company
Rev. 4/06 F068B

Repackaged by:

Rebel Distributors Corp

Thousand Oaks, CA 91320

Patient's Instructions for Use

Before using your Albuterol Inhalation Aerosol, read complete instructions carefully.

Children should use Albuterol Inhalation Aerosol under adult supervision, as instructed by the patient's doctor.

The blue adapter supplied with Albuterol Inhalation Aerosol should not be used with any other product canisters, and adapters from other products should not be used with an Albuterol Inhalation Aerosol canister.

The refill canister is to be used only with the blue Albuterol Inhalation Aerosol adapter ID#720.

- 1.SHAKE THE INHALER WELL immediately before each use. Then remove the cap from the mouthpiece. Should the cap be dislodged or lost, the inhaler mouthpiece should be inspected for the presence of foreign objects before each use. Make sure the canister is fully and firmly inserted into the actuator.
- 2.BREATHE OUT FULLY THROUGH THE MOUTH, expelling as much air from your lungs as possible. Place the mouthpiece fully into the mouth, holding the inhaler in its upright position (see Figure 1) and closing the lips around it.

- 3.WHILE BREATHING IN DEEPLY AND SLOWLY THROUGH THE MOUTH, FULLY DEPRESS THE TOP OF THE METAL CANISTER with your index finger. (See Figure 2).

- 4.HOLD YOUR BREATH AS LONG AS POSSIBLE. Before breathing out, remove the inhaler from your mouth and release your finger from the canister.
- 5.Wait one minute and SHAKE the inhaler again. Repeat steps 2 through 4 for each inhalation prescribed by your doctor.
- 6.CLEANSE THE INHALER THOROUGHLY AND FREQUENTLY. Remove the metal canister and cleanse the plastic case and cap by rinsing thoroughly in warm, running water, at least once a day. After thoroughly drying the plastic case and cap, gently replace the canister into the case with a twisting motion and put the cap back onto the mouthpiece.
- 7.As with all aerosol medications, it is recommended to "test spray" into the air before using for the first time and in cases where the aerosol has not been used for a prolonged period of time.
- 8.DISCARD THE CANISTER AFTER YOU HAVE USED THE LABELED NUMBER OF INHALATIONS.
  The correct amount of medication in each inhalation cannot be assured after 200 actuations, even though the canister is not completely empty. The canister should be discarded when the labeled number of actuations have been used. Before you reach the specific number of actuations, you should consult your doctor to determine whether a refill is needed. Just as you should not take extra doses without consulting your doctor, you also should not stop using Albuterol Inhalation Aerosol without consulting your doctor.

BOXED WARNING

DOSAGE

Use only as directed by your doctor.

WARNINGS

The action of Albuterol Inhalation Aerosol may last up to 6 hours or longer. Albuterol Inhalation Aerosol should not be used more frequently than recommended. Do not increase the dose or frequency of Albuterol Inhalation Aerosol without consulting your doctor. If you find that treatment with Albuterol Inhalation Aerosol becomes less effective for symptomatic relief, your symptoms become worse, and/or you need to use the product more frequently than usual, you should seek medical attention immediately. While you are using Albuterol Inhalation Aerosol, other inhaled drugs and asthma medicines should be used only as directed by your doctor.

Contents Under Pressure. Do not puncture. Do not use or store near heat or open flame. Exposure to temperatures above 120°F may cause bursting. Never throw container into fire or incinerator. Keep out of reach of children. Avoid spraying in eyes.

Store between 15° – 30°C (59°– 86°F). As with most inhaled medications in aerosol canisters, the therapeutic effect of this medication may decrease when the canister is cold; for best results, the canister should be at room temperature before use.

Shake well before using.

Note: The indented statement below is required by the Federal government Clean Air Act for all products containing chlorofluorocarbons (CFC's).

This product contains trichloromonofluoromethane and dichlorodifluoromethane (CFC's), substances which harm the environment by depleting ozone in the upper atmosphere.

Your doctor has determined that this product is likely to help your personal health. USE THIS PRODUCT AS DIRECTED, UNLESS INSTRUCTED TO DO OTHERWISE BY YOUR DOCTOR. If you have any questions about alternatives, consult your doctor.

Manufactured by

Armstrong Pharmaceuticals, Inc.
West Roxbury, MA 02132
An Amphastar Company
Rev. 4/06 F068B

Repackaged by:

Rebel Distributors Corp

Thousand Oaks, CA 91320